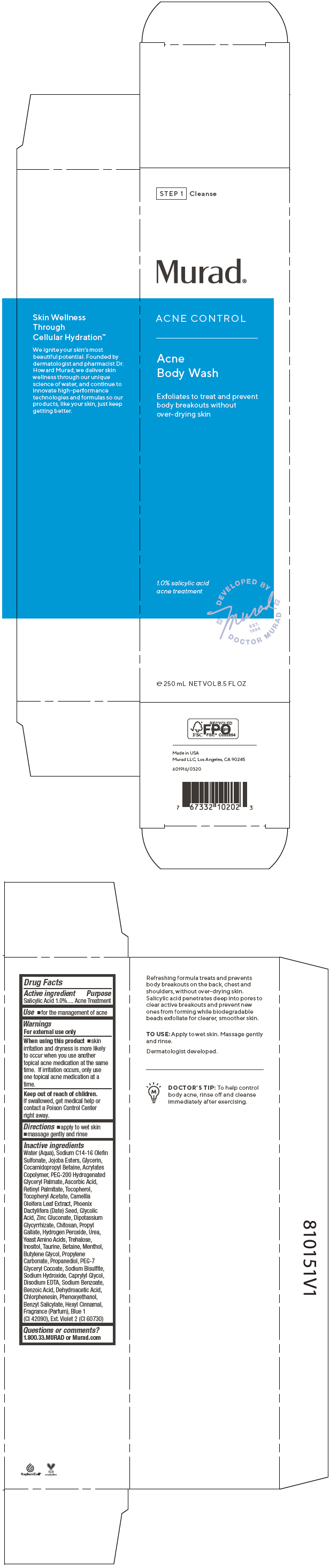 DRUG LABEL: Acne Control Acne Body Wash
NDC: 70381-111 | Form: SOLUTION
Manufacturer: Murad, LLC
Category: otc | Type: HUMAN OTC DRUG LABEL
Date: 20210702

ACTIVE INGREDIENTS: SALICYLIC ACID 1 g/100 mL
INACTIVE INGREDIENTS: WATER; SODIUM C14-16 OLEFIN SULFONATE; HYDROGENATED JOJOBA OIL, RANDOMIZED; GLYCERIN; COCAMIDOPROPYL BETAINE; METHACRYLIC ACID - ETHYL ACRYLATE COPOLYMER (4500 MPA.S); PEG-200 HYDROGENATED GLYCERYL PALMATE; ASCORBIC ACID; VITAMIN A PALMITATE; TOCOPHEROL; .ALPHA.-TOCOPHEROL ACETATE; CAMELLIA OLEIFERA LEAF; PHOENIX DACTYLIFERA SEED; GLYCOLIC ACID; ZINC GLUCONATE; GLYCYRRHIZINATE DIPOTASSIUM; POLIGLUSAM; PROPYL GALLATE; HYDROGEN PEROXIDE; UREA; AMINO ACIDS, SOURCE UNSPECIFIED; TREHALOSE; INOSITOL; TAURINE; BETAINE; MENTHOL, UNSPECIFIED FORM; BUTYLENE GLYCOL; PROPYLENE CARBONATE; PROPANEDIOL; PEG-7 GLYCERYL COCOATE; SODIUM BISULFITE; SODIUM HYDROXIDE; CAPRYLYL GLYCOL; EDETATE DISODIUM ANHYDROUS; SODIUM BENZOATE; BENZOIC ACID; DEHYDROACETIC ACID; CHLORPHENESIN; PHENOXYETHANOL; BENZYL SALICYLATE; .ALPHA.-HEXYLCINNAMALDEHYDE; FD&C BLUE NO. 1; EXT. D&C VIOLET NO. 2

Acne Control Acne Body Wash

Drug Facts

Active ingredient

Salicylic Acid 1.0%

Purpose

Acne Treatment

Use

- for the management of acne

Warnings

For external use only

When using this product

- skin irritation and dryness is more likely to occur when you use another topical acne medication at the same time. If irritation occurs, only use one topical acne medication at a time.

Keep out of reach of children.

If swallowed, get medical help or contact a Poison Control Center right away.

Directions

- apply to wet skin
- massage gently and rinse

Inactive ingredients

Water (Aqua), Sodium C14-16 Olefin Sulfonate, Jojoba Esters, Glycerin, Cocamidopropyl Betaine, Acrylates Copolymer, PEG-200 Hydrogenated Glyceryl Palmate, Ascorbic Acid, Retinyl Palmitate, Tocopherol, Tocopheryl Acetate, Camellia Oleifera Leaf Extract, Phoenix Dactylifera (Date) Seed, Glycolic Acid, Zinc Gluconate, Dipotassium Glycyrrhizate, Chitosan, Propyl Gallate, Hydrogen Peroxide, Urea, Yeast Amino Acids, Trehalose, Inositol, Taurine, Betaine, Menthol, Butylene Glycol, Propylene Carbonate, Propanediol, PEG-7 Glyceryl Cocoate, Sodium Bisulfite, Sodium Hydroxide, Caprylyl Glycol, Disodium EDTA, Sodium Benzoate, Benzoic Acid, Dehydroacetic Acid, Chlorphenesin, Phenoxyethanol, Benzyl Salicylate, Hexyl Cinnamal, Fragrance (Parfum), Blue 1 (CI 42090), Ext. Violet 2 (CI 60730)

Questions or comments?

1.800.33.MURAD or Murad.com

PRINCIPAL DISPLAY PANEL - 250 mL Tube Carton

STEP 1
Cleanse

Murad®

ACNE CONTROL

Acne
Body Wash

Exfoliates to treat and prevent
body breakouts without
over-drying skin

1.0% salicylic acid
acne treatment

DEVELOPED BY
+ Murad +
EST.
1989
DOCTOR MURAD

℮ 250 mL NET VOL 8.5 FL OZ